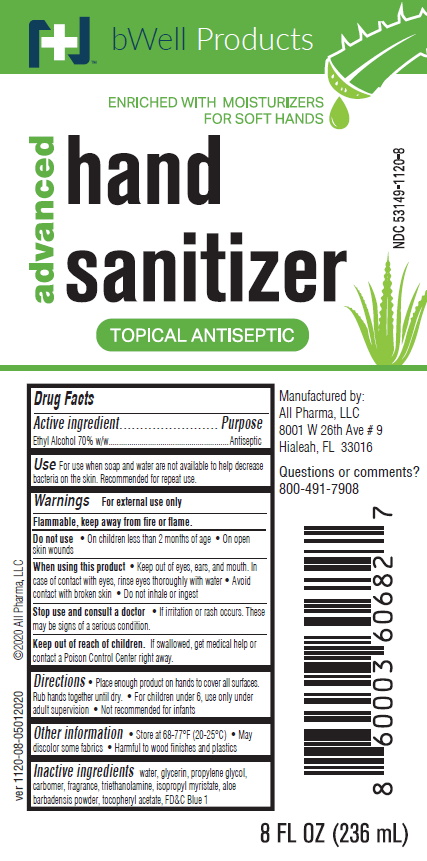 DRUG LABEL: ADVANCE HAND SANITIZER MOISTURIZING FORMULA WITH ALOE AND VITAMIN E
NDC: 53149-1120 | Form: GEL
Manufacturer: All Pharma LLC
Category: otc | Type: HUMAN OTC DRUG LABEL
Date: 20200101

ACTIVE INGREDIENTS: ALCOHOL 70 mL/100 mL
INACTIVE INGREDIENTS: WATER; CARBOMER 980; GLYCERIN; PROPYLENE GLYCOL; ISOPROPYL MYRISTATE; ALOE VERA LEAF; TROLAMINE; FD&C BLUE NO. 1; ALPHA-TOCOPHEROL ACETATE

Active ingredient

Ethyl Alcohol 70.0%

Purpose

Antimicrobial

Uses

To help decrease bacteria on the skin. Recommended for repeat use.

Warnings

For external use only.

WARNINGS

Flammable. Keep away from heat and flame.

When using this product

• Keep out of eyes. In case of contact, rinse eyes thoroughly with water

• Avoid contact with broken skin

• Do not inhale or ingest

Stop use and ask a doctor if

If irritation or redness develops.

Keep out of reach of children.

If swallowed, get medical help or contact a Poison Control Center right away.

Directions

• Wet hands thoroughly with product and allow to dry without wiping
• For children under 6, use only under adult supervision
• Not recommended for infants

Inactive ingredients

water, glycerin, propylene glycol,carbomer, fragrance, triethanolamine, isopropyl myristate, aloe barbadensis powder, tocopheryl acetate, FD&C Blue 1